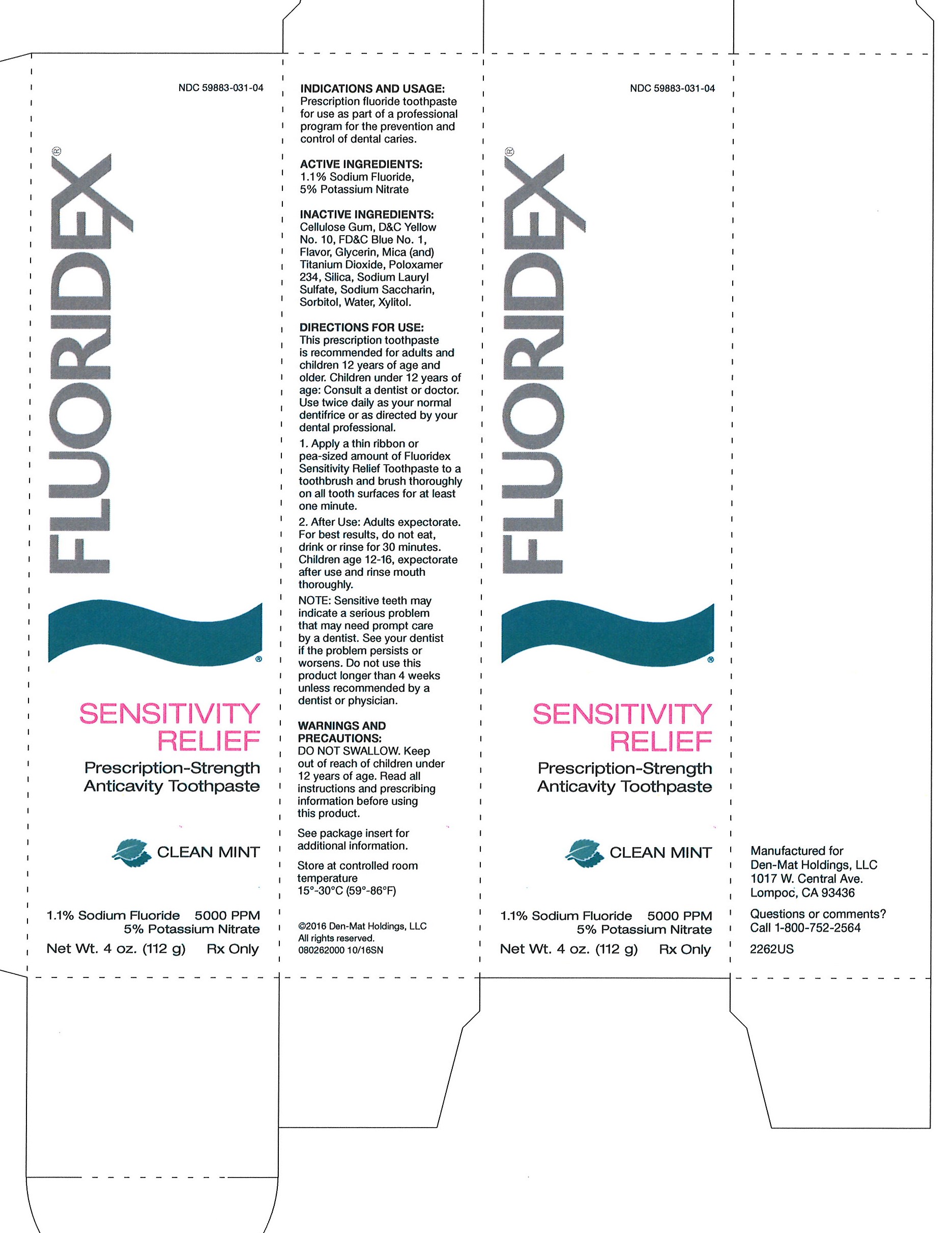 DRUG LABEL: FLUORIDEX
NDC: 59883-031 | Form: PASTE, DENTIFRICE
Manufacturer: DENT-MAT HOLDINGS, LLC.
Category: prescription | Type: HUMAN PRESCRIPTION DRUG LABEL
Date: 20250130

ACTIVE INGREDIENTS: POTASSIUM NITRATE 50 mg/1 g; SODIUM FLUORIDE 5 mg/1 g

Den-Mat Sensitive Toothpaste

HIGHLIGHTS OF PRESCRIBING INFORMATION

HIGHLIGHTS OF PRESCRIBING INFORMATION____________________________

These highlights do not include all the information needed to use Fluoridex toothpaste safely and effectively. See full prescribing information.

Fluoridex 1.1% Sodium Fluoride toothpaste for oral use

INDICATIONS AND USAGE_______________________________________________

Fluoridex toothpaste is indicated for use as part of a professional program for the prevention and control of dental caries. (1)

DOSAGE AND ADMINISTRATION_________________________________________

• Apply a thin ribbon or pea-sized amount of Fluoridex toothpaste to a toothbrush and brush thoroughly on all tooth surfaces for at least one minute. (2)

• After use, adults should expectorate. For best results, do not eat, drink, or rinse for 30 minutes. Children, age 6-16, should expectorate after use and rinse mouth thoroughly. (2)

• Use twice daily as your normal dentifrice or as directed by your dental professional. (2)

DOSAGE FORMS AND STRENGTHS______________________________________

• Daily Defense Mint: Green toothpaste containing 1.1% Sodium Fluoride (Mint). (3)

• Daily Defense Fruit: Pink toothpaste containing 1.1% Sodium Fluoride (Fruit). (3)

• Enhanced Whitening Mint: Green toothpaste containing 1.1% Sodium Fluoride (Mint). (3)

CONTRAINDICATIONS___________________________________________________

Do not use in children under 6 years of age unless recommended by a dentist or physician. (4)

WARNINGS AND PRECAUTIONS_________________________________________

● DO NOT SWALLOW. (5)

● Keep out of reach of children under 6 years of age. If more than used for brushing is accidentally swallowed, get medical help or contact a Poison Control Center right away. (5)

● Repeated ingestion of high levels of fluoride may cause dental fluorosis. (5)

● Do not use this product longer than 4 weeks unless recommended by a dentist or physician. (5)

ADVERSE REACTIONS___________________________________________________

Allergic reactions and other idiosyncrasies have rarely been reported. (6)

To report SUSPECTED ADVERSE REACTIONS, contact DenMat, at 1-800-752-2564, or FDA at 1-800-FDA-1088 or www.fda.gov/medwatch

1 INDICATIONS AND USAGE

Fluoridex toothpaste is indicated for use as part of a professional program for the prevention and control of dental caries.

2 DOSAGE AND ADMINISTRATION

• Follow these instructions or use as instructed by a dental professional.• Adults and children age 6 or older, apply a thin ribbon or pea-sized amount of Fluoridex toothpaste to a toothbrush and brush thoroughly on all tooth surfaces for at least one minute.

After use:

• Adults should expectorate. For best results, do not eat, drink, or rinse for 30 minutes.

• Children, age 6 to 16, should expectorate after use and rinse mouth thoroughly.

• Use twice daily as your normal dentifrice or as directed by your dental professional.

3 DOSAGE FORMS AND STRENGTHS

• Daily Defense Mint: Green toothpaste containing 1.1% Sodium Fluoride (Mint). (3)

• Daily Defense Fruit: Pink toothpaste containing 1.1% Sodium Fluoride (Fruit). (3)

• Enhanced Whitening Mint: Green toothpaste containing 1.1% Sodium Fluoride (Mint). (3)

4 CONTRAINDICATIONS

Do not use in children under 6 years of age unless recommended by a dentist or physician.

5 WARNINGS AND PRECAUTIONS

DO NOT SWALLOW.

• Keep out of reach of children under 6 years of age. If more than used for brushing is accidentally swallowed, get medical help or contact a Poison Control Center right away.

• Prolonged daily ingestion may result in various degrees of dental fluorosis in children with developing dentition, especially if the water fluoridation exceeds 0.6 ppm, since younger children frequently cannot perform the brushing process without significant swallowing.

• Use in children under age 6 years requires special supervision to prevent repeated swallowing of toothpaste which could cause dental fluorosis.

• Read directions carefully before using.

• Keep out of reach of infants and children.

• Sensitive teeth may indicate a serious problem that may need prompt care by a dentist.

• See your dentist if the problem persists or worsens. Do not use this product longer than 4 weeks unless recommended by a dentist or physician.

6 ADVERSE REACTIONS

Allergic reactions and other idiosyncrasies have rarely been reported.

8 USE IN SPECIFIC POPULATIONS

8.1 Pregnancy

Pregnancy Category B It has been shown that fluoride crosses the placenta of rats, but only 0.01% of the amount administered is incorporated in fetal tissues. Animal studies (rats, mice, rabbits) have shown that fluoride is not a teratogen. Maternal exposure to 12.2 mg fluoride/kg of body weight (rats) or 13.1 mg/kg of body weight (rabbits) did not affect the litter size or fetal weight and did not increase the frequency of skeletal or visceral malformations. There are no adequate or well controlled clinical studies in pregnant women. However, epidemiological studies conducted in areas with high levels of naturally fluoridated water showed no increase in birth defects. Heavy exposure to fluoride during in utero development may result in skeletal fluorosis which becomes evident in childhood.

8.3 Nursing Mothers

It is not known if fluoride is excreted in human milk. However, many drugs are excreted in milk, and caution should be exercised when products containing fluoride are administered to a nursing woman. Reduced milk production was reported in farm-raised fox when the animals were fed a diet containing a high concentration of fluoride (98-137 mg/kg of body weight). No adverse effects on parturition, lactation, or offspring were seen in rats administered fluoride up to 5 mg/kg of body weight.

8.4 Pediatric Use

The use of Fluoridex toothpaste in children age 6-16 as a caries preventive is supported by pioneering clinical studies with 1.1% sodium fluoride gels in mouth trays in students age 11-14 years conducted by Englander, et al.2-4 Safety and effectiveness in pediatric patients below the age of 6 years have not been established. Prescribing physicians and dentists should consider total fluoride exposure (dental care plus food, water, and other sources) when prescribing the product for use in children. Please refer to the CONTRAINDICATIONS and WARNINGS AND PRECAUTIONS sections.

8.5 Geriatric Use

Subjects referenced in clinical studies of 1.1% (w/v) sodium fluoride, included 15 percent age 65 and over, with 1 percent age 75 and over. No overall differences in safety or effectiveness were observed between these subjects and younger subjects. Other reported clinical experience has not identified differences in responses between the elderly and younger clients, but greater sensitivity of some older individuals cannot be ruled out. This drug is known to be substantially excreted by the kidney, and the risk of toxic reactions to this drug may be greater in clients with impaired renal function. Because elderly clients are more likely to have decreased renal function, care should be taken in dose selection, and it may be useful to monitor renal function.

10 OVERDOSAGE

Accidental ingestion of large amounts of fluoride may result in acute burning in the mouth and sore tongue. Nausea, vomiting, and diarrhea may occur soon after ingestion (within 30 minutes) and are accompanied by salivation, hematemesis, and epigastric cramping abdominal pain. These symptoms may persist for 24 hours. If less than 5 mg fluoride/kg body weight (i.e., less than 2.3 mg fluoride/lb body weight) have been ingested, give calcium (e.g., milk) orally to relieve gastrointestinal symptoms and observe for a few hours. If more than 5 mg fluoride/kg body weight (i.e., more than 2.3 mg fluoride/lb body weight) have been ingested, induce vomiting, give orally soluble calcium (e.g., milk, 5% calcium gluconate or calcium lactate solution) and immediately seek medical assistance. For accidental ingestion of more than 15 mg fluoride/kg of body weight (i.e., more than 6.9 mg fluoride/lb body weight), induce vomiting and admit immediately to a hospital facility.

11 DESCRIPTION

Fluoridex toothpaste is a self-applied topical fluoride dentifrice containing 1.1% (w/w) sodium fluoride for the prevention and control of dental caries. Daily Defense Mint: Each gram contains 5 mg of fluoride ion in a neutral pH base, consisting of Cellulose Gum, D&C Yellow No. 10, FD&C Blue No. 1, Flavor, Glycerin, Mica (and) Titanium Dioxide, Poloxamer 234, Silica, Sodium Laurel Sulfate, Sodium Saccharin, Sorbitol, Water, Xylitol.

Daily Defense Fruit: Each gram contains 5 mg of fluoride ion in a neutral pH base, consisting of Cellulose Gum, D&C Red No. 33, Flavor, Glycerin, Mica (and) Titanium Dioxide, Poloxamer 234, Silica, Sodium Laurel Sulfate, Sodium Saccharin, Sorbitol, Water, Xylitol.

Enhanced Whitening Mint: Each gram contains 5 mg of fluoride ion in a neutral pH base, consisting of Cellulose Gum, D&C Yellow No. 10, FD&C Blue No. 1, Flavor, Glycerin, Mica (and) Titanium Dioxide, Poloxamer 234, Silica, Sodium Laurel Sulfate, Sodium Saccharin, Sorbitol, Water, Xylitol.

12 CLINICAL PHARMACOLOGY

A treatment dose (a thin ribbon) of Fluoridex 5000 ppm sodium fluoride toothpaste contains 2.5 mg fluoride. A 4 oz. tube contains 566 mg fluoride.

Frequent topical applications to the teeth with preparations having a relatively high fluoride content increase tooth resistance to acid dissolution and enhance penetration of the fluoride ion into tooth enamel.

13 NONCLINICAL TOXICOLOGY

13.1 Carcinogenesis, Mutagenesis, Impairment of Fertility

In a study conducted in rodents, no carcinogenesis was found in male and female mice and female rats treated with fluoride at dose levels ranging from 4.1 to 9.1 mg/kg of body weight. Equivocal evidence of carcinogenesis was reported in male rats treated with 2.5 and 4.1 mg/kg of body weight. In a second study, no cParcinogenesis was observed in rats, males or females, treated with fluoride up to 11.3 mg/kg of body weight. Epidemiological data provide no credible evidence for an association between fluoride, either naturally occurring or added to drinking water, and risk of human cancer. Fluoride ion is not mutagenic in standard bacterial systems. It has been shown that fluoride ion has potential to induce chromosome aberrations in cultured human and rodent cells at doses much higher than those to which humans are exposed. In vivo data are conflicting. Some studies report chromosome damage in rodents, while other studies using similar protocols report negative results. Potential adverse reproductive effects of fluoride exposure in humans have not been adequately evaluated. Adverse effects on reproduction were reported for rats, mice, fox, and cattle exposed to 100 ppm or greater concentrations of fluoride in their diet or drinking water. Other studies conducted in rats demonstrated that lower concentrations of fluoride (5 mg/kg of body w eight) did not result in impaired fertility and reproductive capabilities.

15 REFERENCES

1. American Dental Association, Council on Dental Therapeutics, Fluoride compounds, In: Accepted Dental Therapeutics, Ed. 40, Chicago, ADA, 405-407, (1984).

2. Englander HR, et al., Clinical Anticaries Effect of Repeated Topical Sodium Fluroide Applications by Mouthpieces, JADA, 75, 638-644, (1967).

3. Englander HR, et al., Residual Anticaries Effect of Repeated Topical Sodium Fluoride Applications by Mouthpieces, JADA, 78, 783-787 (1969).

4. Englander HR, et al: JADA, 83:354-358, 1971.

16 HOW SUPPLIED/STORAGE AND HANDLING

4 oz. (112 g) net wt. tube

• Daily Defense Mint NDC 59883-016-04

• Daily Defense Fruit NDC 59883-015-04

• Enhanced Whitening Mint NDC 59883-020-04

Store at controlled room temperature 15°-30° C (59°-86° F)

Principal Display Panel

NDC59883-031-04

FLUORIDEX

SENSITIVITY

RELIEF

Prescription-Strength

Anticavity Toothpaste

CLEAN MINT

1.1% Sodium Fluoride 5000 PPM

5% Potassium Nitrate

Net Wt. 4 oz. (112 g) Rx Only